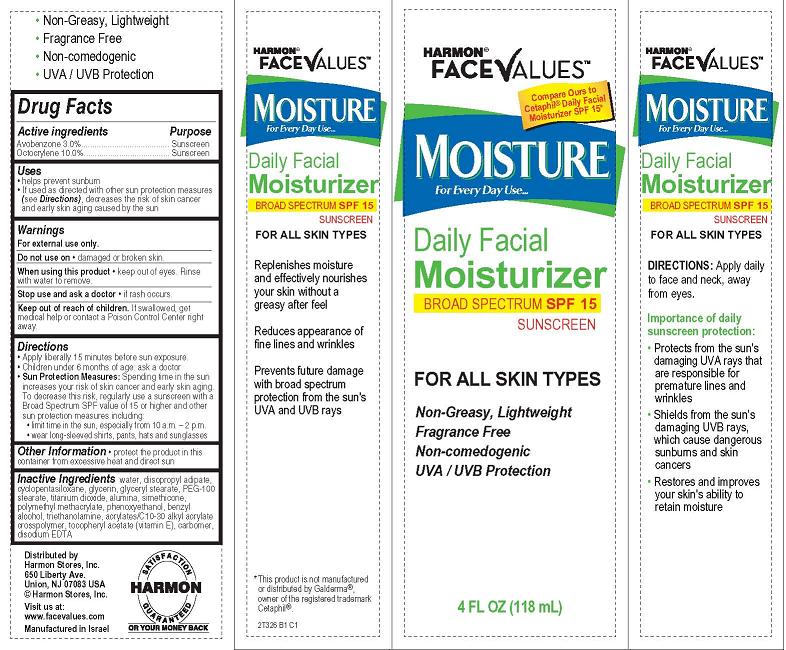 DRUG LABEL: Harmon Face Values Daily Facial
NDC: 63940-000 | Form: CREAM
Manufacturer: Harmon Stores Inc.
Category: otc | Type: HUMAN OTC DRUG LABEL
Date: 20120612

ACTIVE INGREDIENTS: AVOBENZONE 3 mL/100 mL; OCTOCRYLENE 10 mL/100 mL
INACTIVE INGREDIENTS: WATER; DIISOPROPYL ADIPATE; CYCLOMETHICONE 5; GLYCERIN; GLYCERYL MONOSTEARATE; PEG-100 STEARATE; TITANIUM DIOXIDE; ALUMINUM OXIDE; DIMETHICONE; METHYL METHACRYLATE; PHENOXYETHANOL; BENZYL ALCOHOL; TROLAMINE; CARBOMER COPOLYMER TYPE A (ALLYL PENTAERYTHRITOL CROSSLINKED); .ALPHA.-TOCOPHEROL ACETATE; CARBOMER COPOLYMER TYPE B (ALLYL PENTAERYTHRITOL CROSSLINKED); EDETATE DISODIUM

Harmon Face Values Daily Facial Moisturizer Broad Spectrum SPF 15 Sunscreen

Active ingredient

Avobenzone 3.0%

Octocrylene 10.0%

Purpose

Sunscreen

Uses

Helps prevent sunburn

If used as directed with other sun protection measures (see Directions), decreases the risk of skin cancer and early skin aging caused by the sun

Warnings

For external use only.

Do not use on damaged or broken skin.

When using this product keep out of eyes. Rinse with water to remove.

Stop use and ask a doctor if rash occurs.

Keep Out of Reach of Children. If swallowed, get medical help or contact a Poison Control Center right away.

Directions

Apply liberally 15 minutes before sun exposure.

Children under 6 months of age: ask a doctor.

Sun Protection Measures: Spending time in the sun increases your risk of skin cancer and early skin aging. To decrease this risk, regularly use a sunscreen with a Broad Spectrum SPF value of 15 or higher and other sun protection measures including:

- limit time in the sun, especially from 10 a.m. - 2 p.m.
- wear long-sleeved shirts, pants, hats and sunglasses

Inactive ingredients

water, disopropyl adipate, cyclopentasiloxane, glycerin, glyceryl stearate, PEG-100 stearate, titanium dioxide, alumina, simethicone, polymethyl methacrylate, phenoxyethanol, benzyl alcohol, triethanolamine, acrylates/C10-30 aklyl acrylate crosspolymer, tocopheryl acetate (vitamin E), carbomer, disodium EDTA

Package/Label Principal Display Panel

HARMON®
FACEVALUESTM

Daily Facial
Moisturizer
BROAD SPECTRUM SPF 15
SUNSCREEN

FOR ALL SKIN TYPES

Non-Greasy, Lightweight
Fragrance Free
Non-comedogenic
UVA/UVB Protection

Compare Ours to Cetaphil® Daily Facial Moisturizer SPF 15*

4 FL OZ (118 mL)

Distributed by
Harmon Stores, Inc.
650 Liberty Ave.
Union, NJ 07083 USA
Harmon Stores, Inc.
Visit us at:
www.facevalues.com
Manufactured in Israel

Carton Label